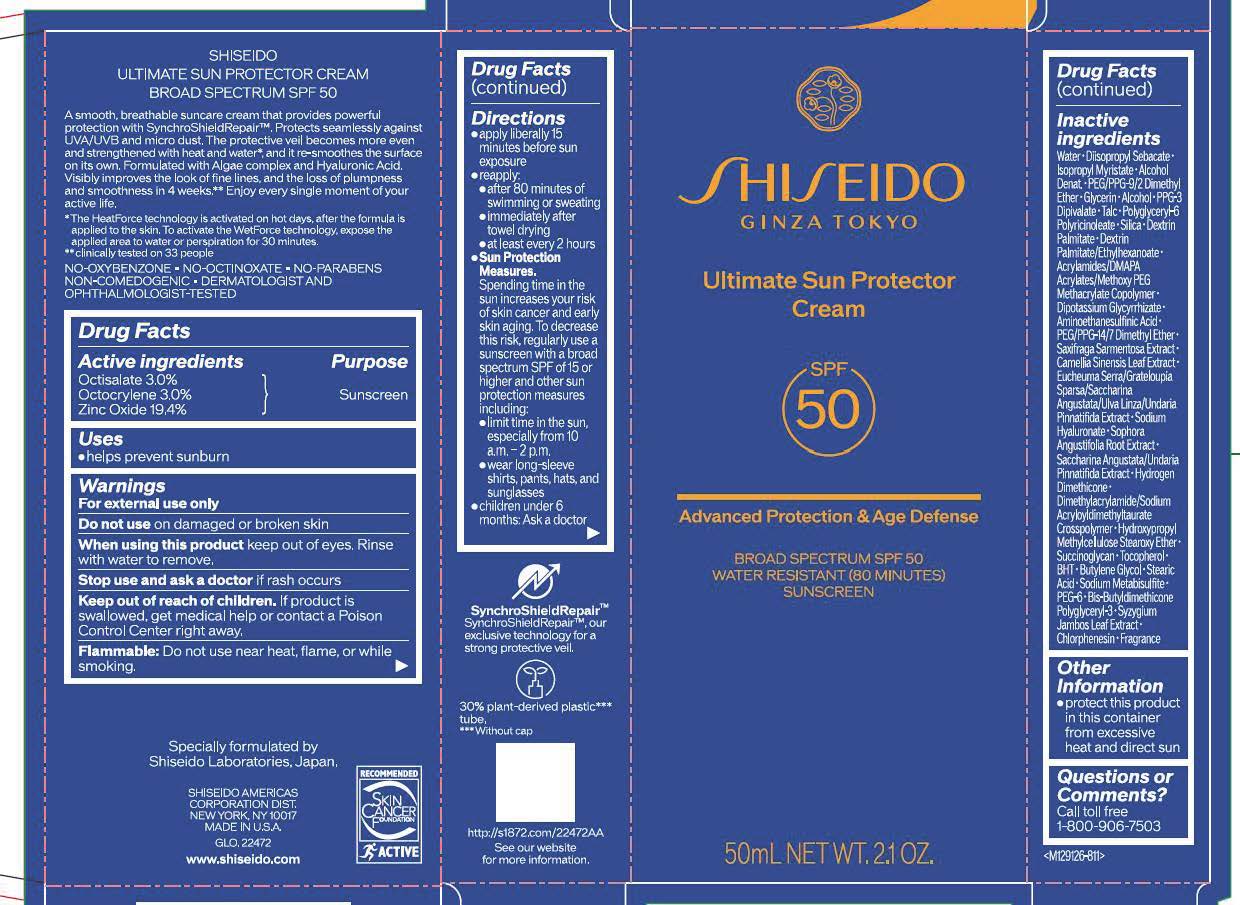 DRUG LABEL: SHISEIDO ULTIMATE SUN PROTECTOR
NDC: 58411-971 | Form: CREAM
Manufacturer: Shiseido Americas Corporation
Category: otc | Type: HUMAN OTC DRUG LABEL
Date: 20260204

ACTIVE INGREDIENTS: OCTOCRYLENE 1.8105 g/50 mL; OCTISALATE 1.8105 g/50 mL; ZINC OXIDE 11.7079 g/50 mL
INACTIVE INGREDIENTS: WATER; DIISOPROPYL SEBACATE; ISOPROPYL MYRISTATE; ALCOHOL; PEG/PPG-9/2 DIMETHYL ETHER; GLYCERIN; TALC; POLYGLYCERYL-6 POLYRICINOLEATE; SILICA; DEXTRIN PALMITATE (CORN; 20000 MW); DIPOTASSIUM GLYCYRRHIZATE; AMINOETHANESULFINIC ACID; PEG/PPG-14/7 DIMETHYL ETHER; SAXIFRAGA STOLONIFERA LEAF; GREEN TEA LEAF; SODIUM HYALURONATE; SOPHORA FLAVESCENS ROOT; HYDROGEN DIMETHICONE (13 CST); HYPROMELLOSE 2208 0.45% STEAROXY ETHER; SUCCINOGLYCAN (AGROBACTERIUM TUMEFACIENS); TOCOPHEROL; BHT; BUTYLENE GLYCOL; STEARIC ACID; SODIUM METABISULFITE; CHLORPHENESIN

SHISEIDO ULTIMATE SUN PROTECTOR

Drug Facts

Active ingredients | Purpose
Octisalate 3.0% | Sunscreen
Octocrylene 3.0% | Sunscreen
Zinc Oxide 19.4% | Sunscreen

Uses

- helps prevent sunburn

Warnings

For external use only

Do not useon damaged or broken skin

WHEN USING

When using this productkeep out of eyes. Rinse with water to remove.

Stop use and ask a doctorif rash occurs

Keep out of reach of children. If product is swallowed, get medical help or contact a Poison Control Center right away.

WARNINGS

Flammable: Do not use near heat, flame, or while smoking.

Directions

- apply liberally 15 minutes before sun exposure
- reapply:
- after 80 minutes of swimming or sweating
- immediately after towel drying
- at least every 2 hours

Sun Protection Measures. Spending time in the sun increases your risk of skin cancer and early skin aging. To decrease this risk, regularly use a sunscreen with a broad spectrum SPF of 15 or higher and other sun protection measures including:

- limit time in the sun, especially from 10 a.m. - 2p.m.
- wear long-sleeve shirts, pant, hats, and sunglasses
- children under 6 months: Ask a doctor

INACTIVE INGREDIENT

WATER･DIISOPROPYL SEBACATE･ISOPROPYL MYRISTATE･ALCOHOL DENAT.･PEG/PPG-9/2 DIMETHYL ETHER･GLYCERIN･ALCOHOL･PPG-3 DIPIVALATE･TALC･POLYGLYCERYL-6 POLYRICINOLEATE･SILICA･DEXTRIN PALMITATE･DEXTRIN PALMITATE/ETHYLHEXANOATE･ACRYLAMIDES/DMAPA ACRYLATES/METHOXY PEG METHACRYLATE COPOLYMER･DIPOTASSIUM GLYCYRRHIZATE･AMINOETHANESULFINIC ACID･PEG/PPG-14/7 DIMETHYL ETHER･SAXIFRAGA SARMENTOSA EXTRACT･CAMELLIA SINENSIS LEAF EXTRACT･EUCHEUMA SERRA/GRATELOUPIA SPARSA/SACCHARINA ANGUSTATA/ULVA LINZA/UNDARIA PINNATIFIDA EXTRACT･SODIUM HYALURONATE･SOPHORA ANGUSTIFOLIA ROOT EXTRACT･SACCHARINA ANGUSTATA/UNDARIA PINNATIFIDA EXTRACT･HYDROGEN DIMETHICONE･DIMETHYLACRYLAMIDE/SODIUM ACRYLOYLDIMETHYLTAURATE CROSSPOLYMER･HYDROXYPROPYL METHYLCELLULOSE STEAROXY ETHER･SUCCINOGLYCAN･TOCOPHEROL･BHT･BUTYLENE GLYCOL･STEARIC ACID･SODIUM METABISULFITE･PEG-6･BIS-BUTYLDIMETHICONE POLYGLYCERYL-3･SYZYGIUM JAMBOS LEAF EXTRACT･CHLORPHENESIN･FRAGRANCE

Other Information

- protect this product in this container from excessive heat and direct sun

Questions or Comments?

Call toll free 1-800-906-7503

Principal Display Panel- 50mL Tube

SHISEIDO

GINZA TOKYO

Ultimate Sun Protector Cream

SPF 50

Advanced Protection & Age Defense

BROAD SPECTRUM SPF 50

WATER RESISTANT (80 MINUTES)

SUNSCREEN